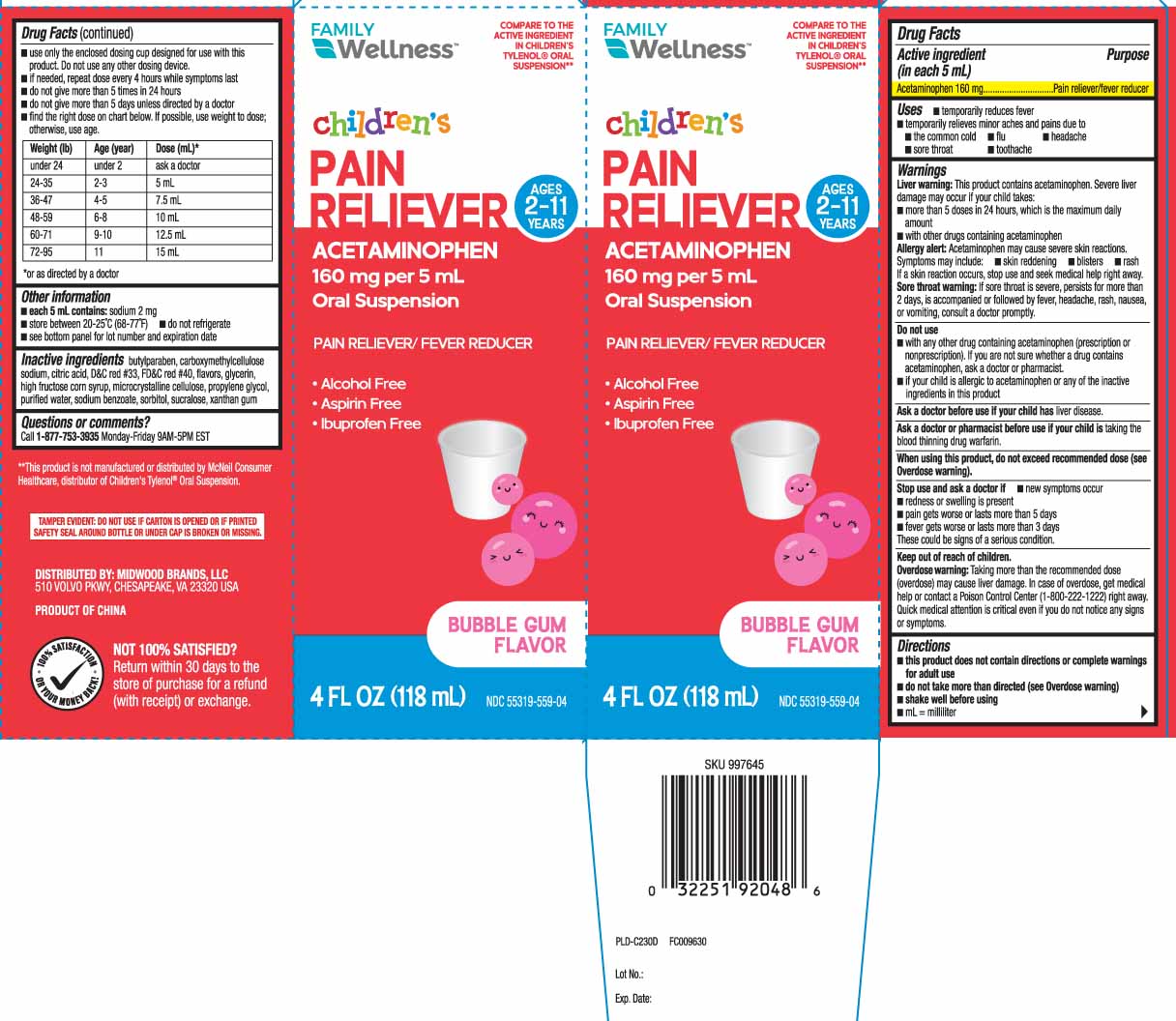 DRUG LABEL: Pain Reliever
NDC: 55319-559 | Form: SUSPENSION
Manufacturer: Family Dollar (FAMILY WELLNESS)
Category: otc | Type: HUMAN OTC DRUG LABEL
Date: 20251003

ACTIVE INGREDIENTS: ACETAMINOPHEN 160 mg/5 mL
INACTIVE INGREDIENTS: ANHYDROUS CITRIC ACID; BUTYLPARABEN; CARBOXYMETHYLCELLULOSE SODIUM; GLYCERIN; HIGH FRUCTOSE CORN SYRUP; CELLULOSE, MICROCRYSTALLINE; PROPYLENE GLYCOL; WATER; SODIUM BENZOATE; SORBITOL; SUCRALOSE; XANTHAN GUM; D&C RED NO. 33; FD&C RED NO. 40

Drug Facts

Active ingredient (in each 5 mL)

Acetaminophen 160 mg

Purpose

Pain reliever/fever reducer

Uses

- temporarily reduces fever
- temporarily relieves minor aches and pains due to:
  - the common cold
  - flu
  - headache
  - sore throat
  - toothache

Warnings

Liver warning: This product contains acetaminophen.Severe liver damage may occur if your child takes:

- more than 5 doses in 24 hours, which is the maximum daily amount
- with other drugs containing acetaminophen

Allergy alert: Acetaminophen may cause severe skin reactions. Symptoms may include:

- skin reddening
- blisters
- rash

If a skin reaction occurs, stop use and seek medical help right away.

Sore throat warning: If sore throat is severe, persists for more than 2 days, is accompanied or followed by fever, headache, rash, nausea, or vomiting, consult a doctor promptly.

Do not use

- with any other drug containing acetaminophen (prescription or non-prescription). If you are not sure whether a drug contains acetaminophen, ask a doctor or pharmacist.
- if your child is allergic to acetaminophen or any of the inactive ingredients in this product

Ask a doctor before use if your child has

liver disease.

Ask a doctor or pharmacist before use if your child is

taking the blood thinning drug warfarin.

When using this product,

do not exceed recommended dose (see overdose warning)

Stop use and ask a doctor if

- new symptoms occur
- redness or swelling is present
- pain gets worse or lasts more than 5 days
- fever gets worse or lasts more than 3 days

These could be signs of a serious condition.

Keep out of reach of children.

Overdose warning: Taking more than the recommended dose (overdose) may cause liver damage. In case of overdose, get medical help or contact a Poison Control Center (1-800-222-1222) right away. Quick medical attention is critical even if you do not notice any signs or symptoms.

Directions

- this product does not contain directions or complete warnings for adult use
- do not take more than directed (see overdose warning)
- shake well before using
- mL = milliliter
- use only the enclosed dosing cup designed for with this product. Do not use any other dosing device.
- if needed, repeat dose every 4 hours while symptoms last
- do not give more than 5 times in 24 hours
- do not give more than 5 days unless directed by a doctor
- find the right dose on chart below. If possible, use weight to dose: otherwise, use age.

Weight (lb) | Age (year) | Dose (mL)*
under 24 | under 2 | ask a doctor
24-35 | 2-3 | 5 mL
36-47 | 4-5 | 7.5 ml
48-59 | 6-8 | 10 mL
60-71 | 9-10 | 12.5 mL
72-95 | 11 | 15 mL

*or as directed by a doctor

Other information

- each 5 mL contains:sodium 2 mg
- store between 20-25ºC (68-77ºF)
- do not refrigerate
- see bottom panel for lot number and expiration date

Inactive ingredients

butylparaben, carboxymethylcellulose sodium, citric acid, D&C red #33, FD&C red #40, flavors, glycerin, high fructose corn syrup, microcrystalline cellulose, propylene glycol, purified water, sodium benzoate, sorbitol, sucralose, xanthan gum

Questions or comments?

Call 1-877-753-3935 Monday-Friday 9AM-5PM EST

Principal Display Panel

COMPARE TO THE ACTIVE INGREDIENT IN CHILDREN'S TYLENOL® ORAL SUSPENSION**

Children's

PAIN RELIEVER

ACETAMINOPHEN 160 mg per 5 mL

Oral suspension

PAIN RELIEVER/FEVER REDUCER

- Aspirin Free
- Alcohol Free
- Ibuprofen Free

AGES 2-11 YEARS

FL OZ (mL)

BUBBLE GUM FLAVOR

**This product is not manufactured or distributed by McNeil Consumer Healthcare, distributor of Children's Tylenol® Oral suspension.

TAMPER EVIDENT: DO NOT USE IF CARTON IS OPENED OR IF PRINTED SAFETY SEAL AROUND BOTTLE OR UNDER CAP IS BROKEN OR MISSING.

DISTRIBUTED BY

MIDWOOD BRANDS LLC

510 VOLVO PKWY,

CHESAPEAKE, VA 23320

Product Label

FAMILY WELLNESS Children's Pain Reliever